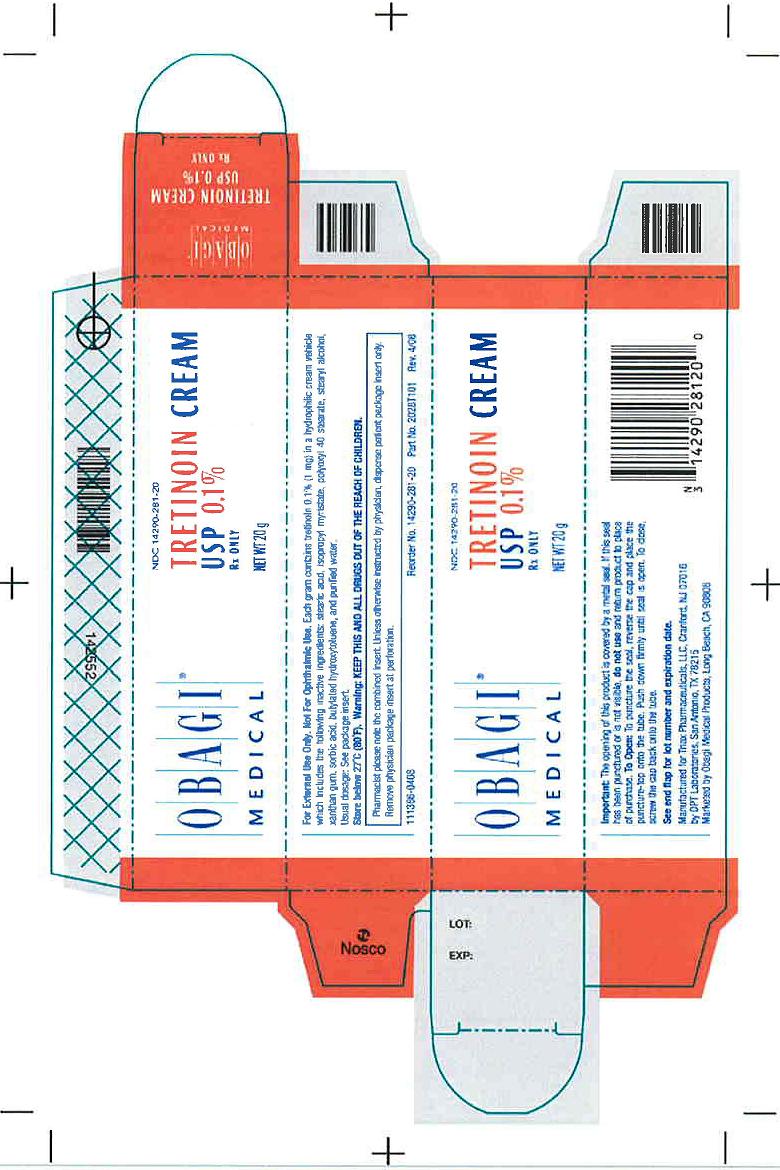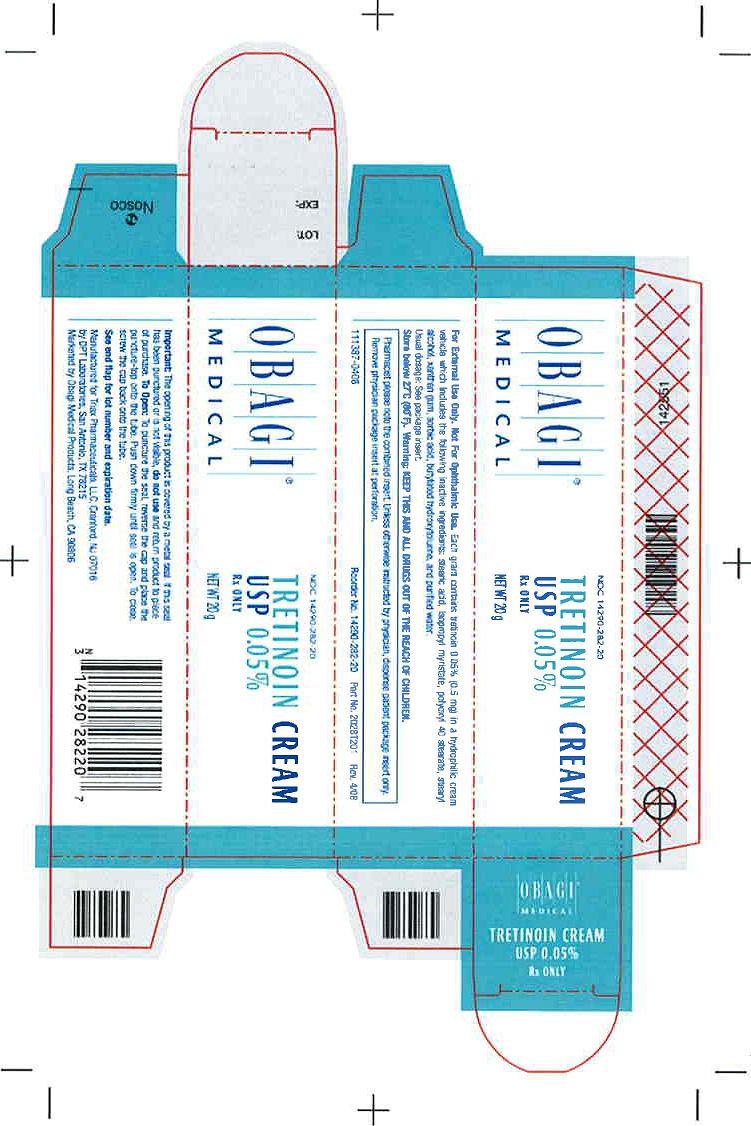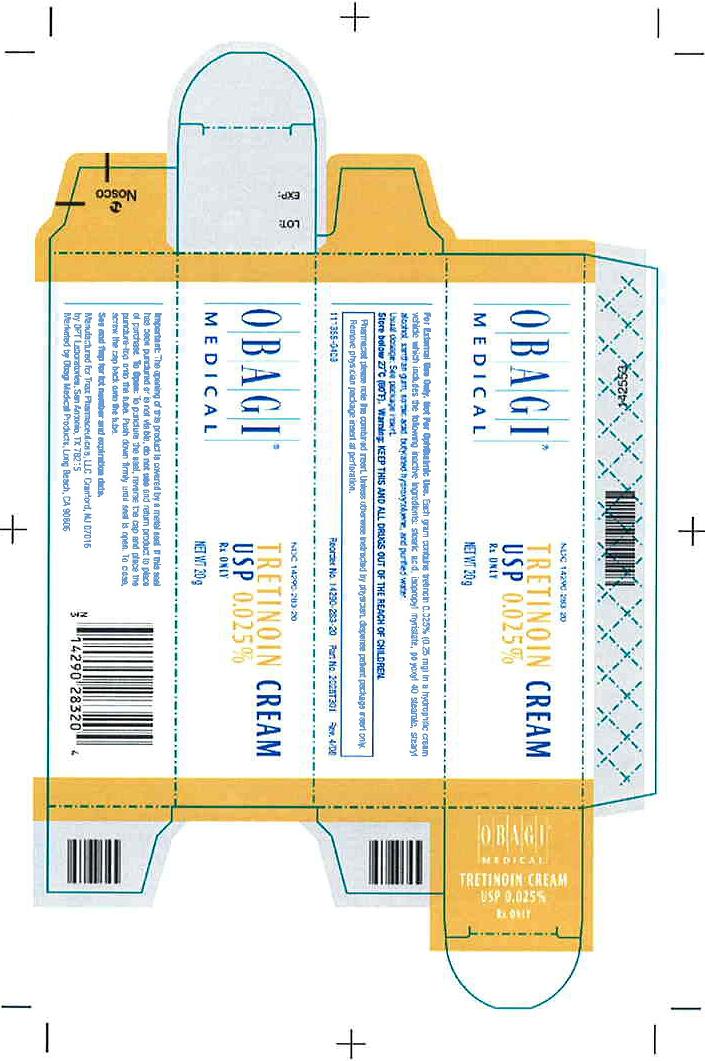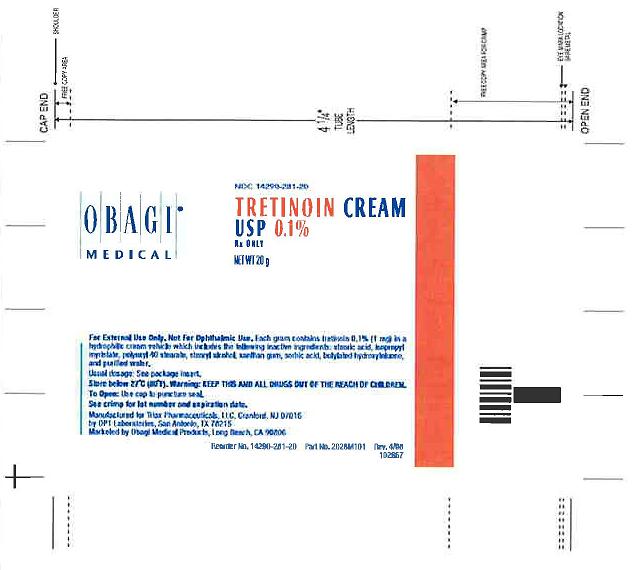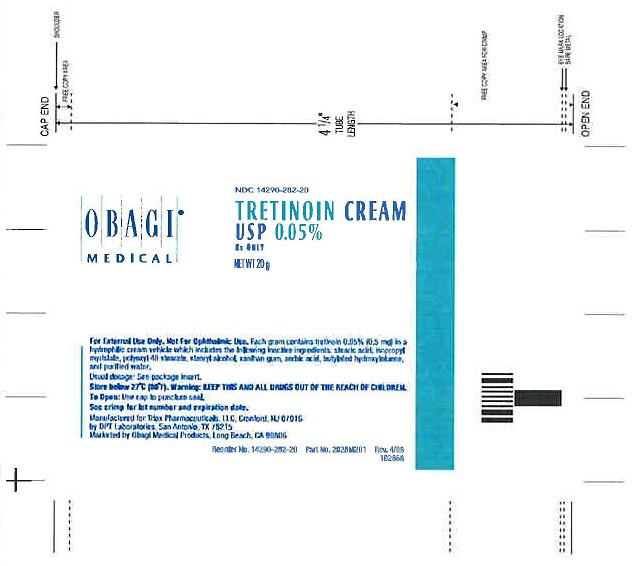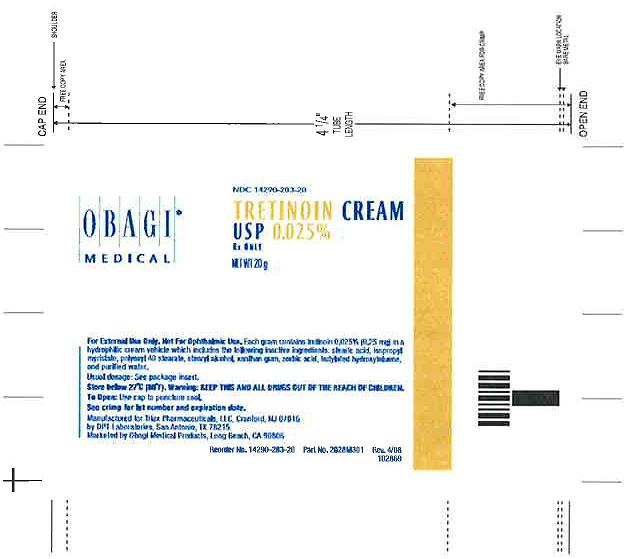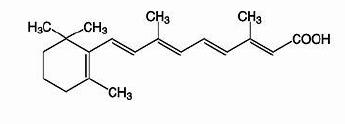 DRUG LABEL: Tretinoin
NDC: 14290-283 | Form: CREAM
Manufacturer: Triax Pharmaceuticals, LLC
Category: prescription | Type: HUMAN PRESCRIPTION DRUG LABEL
Date: 20090715

ACTIVE INGREDIENTS: TRETINOIN 0.25 mg/1 g
INACTIVE INGREDIENTS: XANTHAN GUM; POLYOXYL 40 STEARATE; STEARYL ALCOHOL; STEARIC ACID; ISOPROPYL MYRISTATE; BUTYLATED HYDROXYTOLUENE; SORBIC ACID; WATER; NITROGEN

Tretinoin Gel, USP
Tretinoin Cream, USP
Rx only
For External Use Only.
Not For Ophthalmic Use.

Description

Tretinoin Gel, USP and Tretinoin Cream, USP are used for the topical treatment of acne vulgaris. Each gram of tretinoin gel contains tretinoin in either of two strengths, 0.025% (0.25 mg) or 0.01% (0.1 mg) in a gel vehicle of hydroxypropyl cellulose, butylated hydroxytoluene, and alcohol (denatured with tert-butyl alcohol and brucine sulfate) 90% w/w. Each gram of tretinoin cream contains tretinoin in either of three strengths, 0.1% (1 mg), 0.05% (0.5 mg), or 0.025% (0.25 mg) in a hydrophilic cream vehicle of: stearic acid, isopropyl myristate, polyoxyl 40 stearate, stearyl alcohol, xanthan gum, sorbic acid, butylated hydroxytoluene, and purified water. Chemically, tretinoin is all-trans-retinoic acid. It has a molecular weight of 300.44 and has the following structural formula:

Clinical Pharmacology

Although the exact mode of action of tretinoin is unknown, current evidence suggests that topical tretinoin decreases cohesiveness of follicular epithelial cells with decreased microcomedo formation. Additionally, tretinoin stimulates mitotic activity and increased turnover of follicular epithelial cells causing extrusion of the comedones.

Indications and Usage

Tretinoin gel and cream are indicated for topical application in the treatment of acne vulgaris. The safety and efficacy of the long-term use of this product in the treatment of other disorders have not been established.

Contraindications

Use of the product should be discontinued if hypersensitivity to any of the ingredients is noted.

Warnings

GELS ARE FLAMMABLE. AVOID FIRE, FLAME OR SMOKING DURING USE. Keep out of reach of children. Keep tube tightly closed. Do not expose to heat or store at temperatures above 120°F (49°C).

Precautions

General

If a reaction suggesting sensitivity or chemical irritation occurs, use of the medication should be discontinued. Exposure to sunlight, including sunlamps, should be minimized during the use of tretinoin, and patients with sunburn should be advised not to use the product until fully recovered because of heightened susceptibility to sunlight as a result of the use of tretinoin. Patients who may be required to have considerable sun exposure due to occupation and those with inherent sensitivity to the sun should exercise particular caution. Use of sunscreen products and protective clothing over treated areas is recommended when exposure cannot be avoided. Weather extremes, such as wind or cold, also may be irritating to patients under treatment with tretinoin.

Tretinoin preparations for acne treatment should be kept away from the eyes, the mouth, angles of the nose, and mucous membranes. Topical use may induce severe local erythema and peeling at the site of application. If the degree of local irritation warrants, patients should be directed to use the medication less frequently, discontinue use temporarily, or discontinue use altogether. Tretinoin has been reported to cause severe irritation on eczematous skin and should be used with utmost caution in patients with this condition.

Drug Interactions

Concomitant topical medication, medicated or abrasive soaps and cleansers, soaps and cosmetics that have a strong drying effect, and products with high concentrations of alcohol, astringents, spices or lime should be used with caution because of possible interaction with tretinoin. Particular caution should be exercised in using preparations containing sulfur, resorcinol, or salicylic acid with tretinoin. It also is advisable to "rest" a patient's skin until the effects of such preparations subside before use of tretinoin is begun.

Carcinogenesis, Mutagenesis, Impairment to Fertility

In a 91-week dermal study in which CD-1 mice were administered 0.017% and 0.035% formulations of tretinoin, cutaneous squamous cell carcinomas and papillomas in the treatment area were observed in some female mice. A dose-related incidence of liver tumors in male mice was observed at those same doses. The maximum systemic doses associated with the administered 0.017% and 0.035% formulations are 0.5 and 1.0 mg/kg/day, respectively. These doses are two and four times the maximum human systemic dose, when adjusted for total body surface area. The biological significance of these findings is not clear because they occurred at doses that exceeded the dermal maximally tolerated dose (MTD) of tretinoin and because they were within the background natural occurrence rate for these tumors in this strain of mice. There was no evidence of carcinogenic potential when 0.025 mg/kg/day of tretinoin was administered topically to mice (0.1 times the maximum human systemic dose, adjusted for total body surface area). For purposes of comparisons of the animal exposure to systemic human exposure, the maximum human systemic dose is defined as 1 gram of 0.1% tretinoin applied daily to a 50 kg person (0.02 mg tretinoin/kg body weight).

Studies in hairless albino mice suggest that concurrent exposure to tretinoin may enhance the tumorigenic potential of carcinogenic doses of UVB and UVA light form a solar simulator. This effect has been confirmed in a later study in pigmented mice, and dark pigmentation did not overcome the enhancement of photocarcinogenesis by 0.05% tretinoin. Although the significance of these studies to humans is not clear, patients should minimize exposure to sunlight or artificial ultraviolet irradiation sources.

The mutagenic potential of tretinoin was evaluated in the Ames assay and in the in vivo mouse micronucleus assay, both of which were negative.

In dermal Segment I fertility studies of tretinoin in rats, slight (not statistically significant) decreases in sperm count and motility were seen at 0.5 mg/kg/day (4 times the maximum human systemic dose adjusted for total body surface area), and slight (not statistically significant) increases in the number and percent of nonviable embryos in females treated with 0.25 mg/kg/day (2 times the maximum human systemic dose adjusted for total body surface area) and above were observed. A dermal Segment III study with tretinoin has not been performed in any species. In oral Segment I and Segment III studies in rats with tretinoin, decreased survival of neonates and growth retardation were observed at doses in excess of 2 mg/kg/day (16 times the human topical dose adjusted for total body surface area).

Pregnancy

Teratogenic effects. Pregnancy Category C. Oral tretinoin has been shown to be teratogenic in rats, mice, hamsters, and subhuman primates. It was teratogenic and fetotoxic in Wistar rats when given orally or topically in doses greater than 1 mg/kg/day (8 times the maximum human systemic dose adjusted for total body

surface area). However, variations in teratogenic doses among various strains of rats have been reported. In the cynomolgus monkey, which metabolically is closer to humans for tretinoin than the other species examined, fetal malformations were reported at doses of 10 mg/kg/day or greater, but none were observed at 5 mg/kg/day (83 times the maximum human systemic dose adjusted for total body surface area), although increased skeletal variations were observed at all doses. A dose-related increase in embryolethality and abortion was reported. Similar results have also been reported in pigtail macaques.

Topical tretinoin in animal teratogenicity tests has generated equivocal results. There is evidence for teratogenicity (shortened or kinked tail) of topical tretinoin in Wistar rats at doses greater than 1 mg/kg/day (8 times the maximum human systemic dose adjusted for total body surface area). Anomalies (humerus: short 13%, bent 6%, os parietal incompletely ossified 14%) have also been reported when 10 mg/kg/day was topically applied.

There are other reports in New Zealand White rabbits administered doses of greater than 0.2 mg/kg/day (3.3 times the maximum human systemic dose adjusted for total body surface area) of an increased incidence of domed head and hydrocephaly, typical of retinoid-induced fetal malformations in this species.

In contrast, several well-controlled animal studies have shown that dermally applied tretinoin may be fetotoxic, but not overly teratogenic in rats and rabbits at doses of 1.0 and 0.5 mg/kg/day, respectively (8 times the maximum human systemic dose adjusted for total body surface area in both species).

With widespread use of any drug, a small number of birth defect reports associated temporally with the administration of the drug would be expected by chance alone. Thirty human cases of temporally associated congenital malformations have been reported during two decades of clinical use of tretinoin. Although no definite pattern of teratogenicity and no causal association has been established from these cases, five of the reports describe the rare birth defect category holoprosencephaly (defects associated with incomplete midline development of the forebrain). The significance of these spontaneous reports in terms of risk to the fetus is not known.

Nonteratogenic effects: Topical tretinoin has been shown to be fetotoxic in rabbits when administered 0.5 mg/kg/day (8 times the maximum human systemic dose adjusted for total body surface area). Oral tretinoin has been shown to be fetotoxic, resulting in skeletal variations and increased intrauterine death in rats when administered 2.5 mg/kg/day (20 times the maximum human systemic dose adjusted for total body surface area).

There are no adequate and well-controlled studies in pregnant women. Tretinoin should be used during pregnancy only if the potential benefit justifies the potential risk to the fetus.

NURSING MOTHERS

It is not known whether this drug is excreted in human milk. Because many drugs are excreted in human milk, caution should be exercised when tretinoin is used by a nursing woman.

Pediatric Use

Safety and effectiveness in pediatric patients below the age of 12 have not been established.

Geriatric Use

Safety and effectiveness in a geriatric population have not been established. Clinical studies of tretinoin did not include sufficient numbers of subjects aged 65 and over to determine whether they respond differently from younger patients.

Adverse Reactions

The skin of certain sensitive individuals may become excessively red, edematous, blistered, or crusted. If these effects occur, the medication should either be discontinued until the integrity of the skin is restored, or the medication should be adjusted to a level the patient can tolerate. True contact allergy to topical tretinoin is rarely encountered. Temporary hyper- or hypopigmentation has been reported with repeated application of a tretinoin preparation. Some individuals have been reported to have heightened susceptibility to sunlight while under treatment with tretinoin. To date, all adverse effects of tretinoin have been reversible upon discontinuance of therapy (see Dosage and Administration Section).

Overdosage

If medication is applied excessively, no more rapid or better results will be obtained and marked redness, peeling, or discomfort may occur. Oral ingestion of the drug may lead to the same side effects as those associated with excessive oral intake of Vitamin A.

Dosage and Administration

Tretinoin gel or cream should be applied once a day, before retiring, to the skin where acne lesions appear, using enough to cover the entire affected area lightly. Gel: Excessive application results in "pilling" of the gel, which minimizes the likelihood of over application by the patient.

Application may cause a transitory feeling of warmth or slight stinging. In cases where it has been necessary to temporarily discontinue therapy or to reduce the frequency of application, therapy may be resumed or frequency of application increased when the patients become able to tolerate the treatment.

Alterations of vehicle, drug concentration, or dose frequency should be closely monitored by careful observation of the clinical therapeutic response and skin tolerance.

During the early weeks of therapy, an apparent exacerbation of inflammatory lesions may occur. This is due to the action of the medication on deep, previously unseen lesions and should not be considered a reason to discontinue therapy.

Therapeutic results should be noticed after two to three weeks but more than six weeks of therapy may be required before definite beneficial effects are seen.

Once the acne lesions have responded satisfactorily, it may be possible to maintain the improvement with less frequent applications, or other dosage forms.

Patients treated with tretinoin preparations may use cosmetics, but the areas to be treated should be cleansed thoroughly before the medication is applied (see Precautions).

How Supplied

Tretinoin Cream, USP

NDC CODE Strength Qty.

14290-281-20 0.1% 20 g

14290-282-20 0.05% 20 g

14290-283-20 0.025% 20 g

Storage Conditions

Tretinoin Cream, USP: store below 27°C (80°F)

Manufactured for Triax Pharmaceuticals, LLC,

Cranford, NJ 07016

by DPT Laboratories, San Antonio, TX 78215

Marketed by Obagi Medical Products, Long Beach, CA 90806

Rev. 04/08

128F301

PATIENT INSTRUCTIONS

Acne Treatment

IMPORTANT

Read Directions Carefully Before Using

Read Directions Carefully Before Using.

THIS LEAFLET TELLS YOU ABOUT TRETINOIN ACNE TREATMENT AS PRESCRIBED BY YOUR PHYSICIAN. THIS PRODUCT IS TO BE USED ONLY ACCORDING TO YOUR DOCTOR'S INSTRUCTIONS, AND IT SHOULD NOT BE APPLIED TO OTHER AREAS OF THE BODY OR TO OTHER GROWTHS OR LESIONS. THE LONG-TERM SAFETY AND EFFECTIVENESS OF THIS PRODUCT IN OTHER DISORDERS HAVE NOT BEEN EVALUATED. IF YOU HAVE ANY QUESTIONS, BE SURE TO ASK YOUR DOCTOR.

WARNINGS

TRETINOIN GELS ARE FLAMMABLE. AVOID FIRE, FLAME OR SMOKING DURING USE. Keep out of reach of children. Keep tube tightly closed. Do not expose to heat or store at temperatures above 120°F (49° C).

PRECAUTIONS

The effects of the sun on your skin. As you know, overexposure to natural sunlight or the artificial sunlight of a sunlamp can cause sunburn. Overexposure to the sun over many years may cause premature aging of the skin and even skin cancer. The chances of these effects occurring will vary depending on skin type, the climate and the care taken to avoid overexposure to the sun. Therapy with tretinoin may make your skin more susceptible to sunburn and other adverse effects of the sun, so unprotected exposure to natural or artificial sunlight should be minimized.

Laboratory findings. When laboratory mice are exposed to artificial sunlight, they often develop skin tumors. These sunlight-induced tumors may appear more quickly and in greater number if the mouse is also topically treated with the active ingredient tretinoin. In some studies, under different conditions, however, when mice treated with tretinoin were exposed to artificial sunlight, the incidence and rate of development of skin tumors was reduced. There is no evidence to date that tretinoin alone will cause the development of skin tumors in either laboratory animals or humans. However, investigations in this area are continuing.

Use caution in the sun. When outside, even on hazy days, areas treated with tretinoin should be protected. An effective sunscreen should be used any time you are outside (consult your physician for a recommendation of an SPF level which will provide you with the necessary high level of protection). For extended sun exposure, protective clothing, like a hat, should be worn. Do not use artificial sunlamps while you are using tretinoin. If you do become sunburned, stop your therapy with tretinoin until your skin has recovered.

Avoid excessive exposure to wind or cold. Extremes of climate tend to dry or burn normal skin. Skin treated with tretinoin may be more vulnerable to these extremes. Your physician can recommend ways to manage your acne treatment under such conditions.

Possible problems. The skin of certain sensitive individuals may become excessively red, swollen, blistered or crusted. If you are experiencing severe or persistent irritation, discontinue the use of tretinoin and consult your physician.

There have been reports that, in some patients, areas treated with tretinoin developed a temporary increase or decrease in the amount of skin pigment (color) present. The pigment in these areas returned to normal either when the skin was allowed to adjust to tretinoin or therapy was discontinued.

Use other medication only on your doctor's advice. Only your physician knows which other medications may be helpful during treatment and will recommend them to you if necessary. Follow the physician's instructions carefully. In addition, you should avoid preparations that may dry or irritate your skin. These preparations may include certain astringents, toiletries containing alcohol, spices or lime, or certain medicated soaps, shampoos and hair permanent solutions. Do not allow anyone else to use this medication.

Do not use other medications with tretinoin which are not recommended by your doctor. The medications you have used in the past might cause unnecessary redness or peeling.

If you are pregnant, think you are pregnant or are nursing an infant: No studies have been conducted in humans to establish the safety of tretinoin in pregnant women. If you are pregnant, think you are pregnant, or are nursing a baby, consult your physician before using this medication.

AND WHILE YOU'RE ON TRETINOIN THERAPY

Use a mild, non-medicated soap. Avoid frequent washings and harsh scrubbing. Acne isn't caused by dirt, so no matter how hard you scrub, you can't wash it away. Washing too frequently or scrubbing too roughly may at times actually make your acne worse. Wash your skin gently with a mild, bland soap. Two or three times a day should be sufficient. Pat skin dry with a towel. Let the face dry 20-30 minutes before applying tretinoin. Remember, excessive irritation such as rubbing, too much washing, use of other medications not suggested by your physician, etc., may worsen your acne.

HOW TO USE TRETINOIN

To get the best results with tretinoin therapy, it is necessary to use it properly. Forget about the instructions given for other products and the advice of friends. Just stick to the special plan your doctor has laid out for you and be patient. Remember, when tretinoin is used properly, many users see improvement by 12 weeks. AGAIN, FOLLOW INSTRUCTIONS — BE PATIENT — DON'T START AND STOP THERAPY ON YOUR OWN — IF YOU HAVE QUESTIONS, ASK YOUR DOCTOR.

To help you use the medication correctly, keep these simple instructions in mind.

• Apply tretinoin once daily before bedtime, or as directed by your physician. Your physician may advise, especially if your skin is sensitive, that you start your therapy by applying tretinoin every other night. First, wash with a mild soap and dry your skin gently. WAIT 20 to 30 MINUTES BEFORE APPLYING MEDICATION; it is important for skin to be completely dry in order to minimize possible irritation.

• It is better not to use more than the amount suggested by your physician or to apply more frequently than instructed. Too much may irritate the skin, waste medication and won't give faster or better results.

• Keep the medication away from the corners of the nose, mouth, eyes, and open wounds. Spread away from these areas when applying.

• Tretinoin Cream: Squeeze about a half inch or less of medication onto the fingertip. While that should be enough for your whole face, after you have some experience with the medication you may find you need slightly more or less to do the job. The medication should become invisible almost immediately. If it is still visible, you are using too much. Cover the affected area lightly with tretinoin cream by first dabbing it on your forehead, chin and both cheeks, then spreading it over the entire affected area. Smooth gently into the skin.

• Tretinoin Gel: Squeeze about a half inch or less of medication onto the fingertip While that should be enough for your whole face, after you have some experience with the medication you may find you need slightly more or less to do the job. The medication should become invisible almost immediately. If it is still visible, or if dry flaking occurs from the gel within a minute or so, you are using too much. Cover the affected area lightly with tretinoin gel by first dabbing it on your forehead, chin and both cheeks, then spreading it over the entire affected area. Smooth gently into the skin.

• It is recommended that you apply a moisturizer or a moisturizer with sunscreen that will not aggravate your acne (noncomedogenic) every morning after you wash.

WHAT TO EXPECT WITH YOUR NEW TREATMENT

Tretinoin works deep inside your skin and this takes time. You cannot make tretinoin work any faster by applying more than one dose each day, but an excess amount of tretinoin may irritate your skin. Be patient.

There may be some discomfort or peeling during the early days of treatment. Some patients also notice that their skin begins to take on a blush.

These reactions do not happen to everyone. If they do, it is just your skin adjusting to tretinoin and this usually subsides within two to four weeks. These reactions can usually be minimized by following instructions carefully. Should the effects become excessively troublesome, consult your doctor.

BY THREE TO SIX WEEKS, some patients notice an appearance of new blemishes (papules and pustules). At this stage it is important to continue using tretinoin.

If tretinoin is going to have a beneficial effect for you, you should notice a continued improvement in your appearance after 6 to 12 weeks of therapy. Don't be discouraged if you see no immediate improvement. Don't stop treatment at the first signs of improvement.

Once your acne is under control you should continue regular application of tretinoin until your physician instructs otherwise.

IF YOU HAVE QUESTIONS

All questions of a medical nature should be taken up with your doctor. For more information about tretinoin, call our toll-free number: 866-48-TRIAX (87429). Call between 9:00 a.m. and 3:00 p.m. Eastern Time, Monday through Friday.

Manufactured for Triax Pharmaceuticals, LLC,

Cranford, NJ 07016

by DPT Laboratories, San Antonio, TX 78215

Marketed by Obagi Medical Products, Long Beach, CA 90806

Rev. 04/08

128F301

PRINCIPAL DISPLAY PANEL

NDC 14290-281-20

NDC 14290-282-20

NDC 14290-283-20